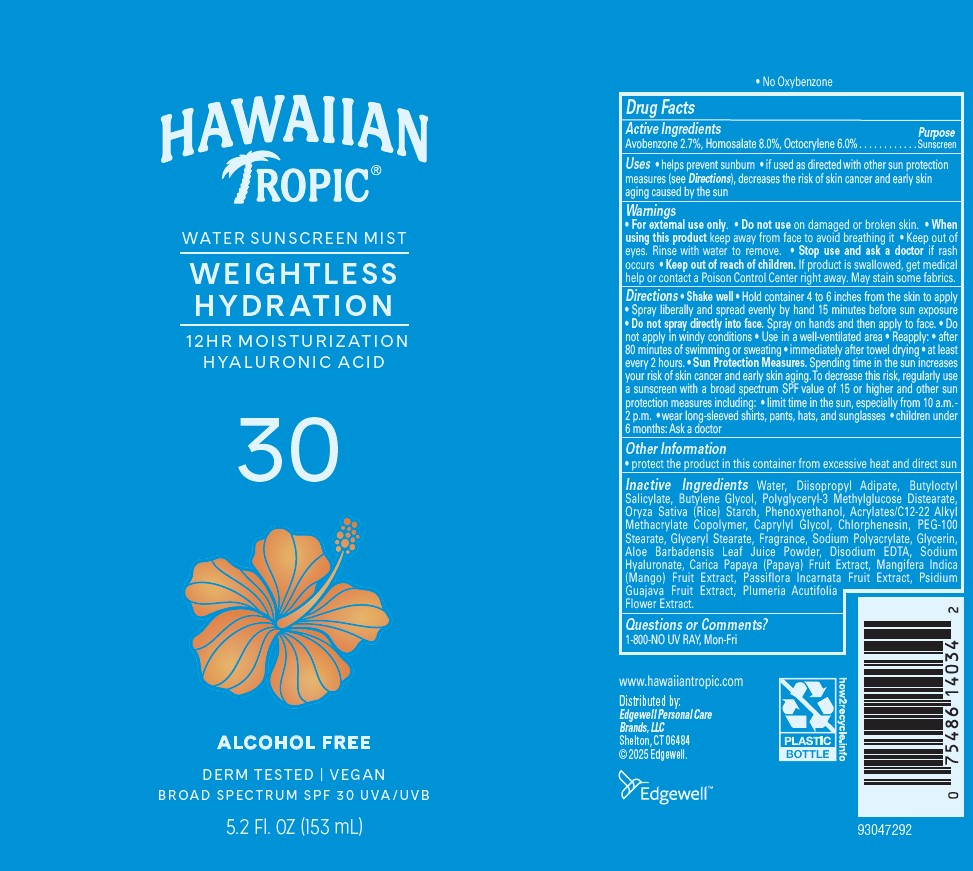 DRUG LABEL: HAWAIIAN TROPIC
NDC: 63354-324 | Form: SPRAY
Manufacturer: Edgewell Personal Care Brands LLC
Category: otc | Type: HUMAN OTC DRUG LABEL
Date: 20251230

ACTIVE INGREDIENTS: HOMOSALATE 8 g/100 g; OCTOCRYLENE 6 g/100 g; AVOBENZONE 2.7 g/100 g
INACTIVE INGREDIENTS: DIISOPROPYL ADIPATE; POLYGLYCERYL-3 METHYLGLUCOSE DISTEARATE; GLYCERYL MONOSTEARATE; EDETATE DISODIUM; PAPAYA; PASSIFLORA INCARNATA FRUIT; CAPRYLYL GLYCOL; CHLORPHENESIN; SODIUM POLYACRYLATE (2500000 MW); HYALURONATE SODIUM; GUAVA; PLUMERIA RUBRA FLOWER; WATER; STARCH, RICE; PHENOXYETHANOL; PEG-100 STEARATE; ALOE VERA LEAF; BUTYLENE GLYCOL; MANGO; GLYCERIN; BUTYLOCTYL SALICYLATE

Active Ingredient

Avobenzone 2.7%, Homosalate 8.0%, Octocrylene 6.0%

Purpose

Sunscreen

Uses

• helps prevent sunburn • if used as directed with other sun protection measures (see Directions), decreases the risk of skin cancer and early skin aging caused by the sun

Warnings

For external use only

Do not use

on damaged or broken skin.

When using this product

keep away from face to avoid breathing it • Keep out of eyes. Rinse with water to remove.

Stop use and ask a doctor

if rash occurs

Keep out of reach of children.

If product is swallowed, get medical help or contact a Poison Control Center right away.

Directions

• Shake well • Hold container 4 to 6 inches from the skin to apply • Spray liberally and spread evenly by hand 15 minutes before sun exposure • Do not spray directly into face. Spray on hands and then apply to face. • Do not apply in windy conditions • Use in a well-ventilated area • Reapply: • after 80 minutes of swimming or sweating • immediately after towel drying • at least every 2 hours.
• Sun Protection Measures. Spending time in the sun increases your risk of skin cancer and early skin aging. To decrease this risk, regularly use a sunscreen with a broad spectrum SPF value of 15 or higher and other sun protection measures including: • limit time in the sun, especially from 10 a.m. - 2 p.m. • wear long-sleeved shirts, pants, hats, and sunglasses • children under 6 months: Ask a doctor

Inactive Ingredients

Water, Diisopropyl Adipate, Butyloctyl Salicylate, Butylene Glycol, Polyglyceryl-3 Methylglucose Distearate, Oryza Sativa (Rice) Starch, Phenoxyethanol, Acrylates/C12-22 Alkyl Methacrylate Copolymer, Caprylyl Glycol, Chlorphenesin, PEG-100 Stearate, Glyceryl Stearate, Fragrance, Sodium Polyacrylate, Glycerin, Aloe Barbadensis Leaf Juice Powder, Disodium EDTA, Sodium Hyaluronate, Carica Papaya (Papaya) Fruit Extract, Mangifera Indica (Mango) Fruit Extract, Passiflora Incarnata Fruit Extract, Psidium Guajava Fruit Extract, Plumeria Acutifolia Flower Extract.

Other Information

Protect this product from excessive heat and direct sun

Questions or Comments?

1-800-NO UV RAY, Mon-Fri

Principal Display Panel

HAWAIIAN TROPIC

WATER SUNSCREEN MIST

WEIGHTLESS

HYDRATION

12 HR MOISTURIZATION

HYALURONIC ACID

30

ALCOHOL FREE

DERM TESTED | VEGAN

BROAD SPECTRUM SPF 30 UVA/UVB

5. Fl. OZ (153 ml)